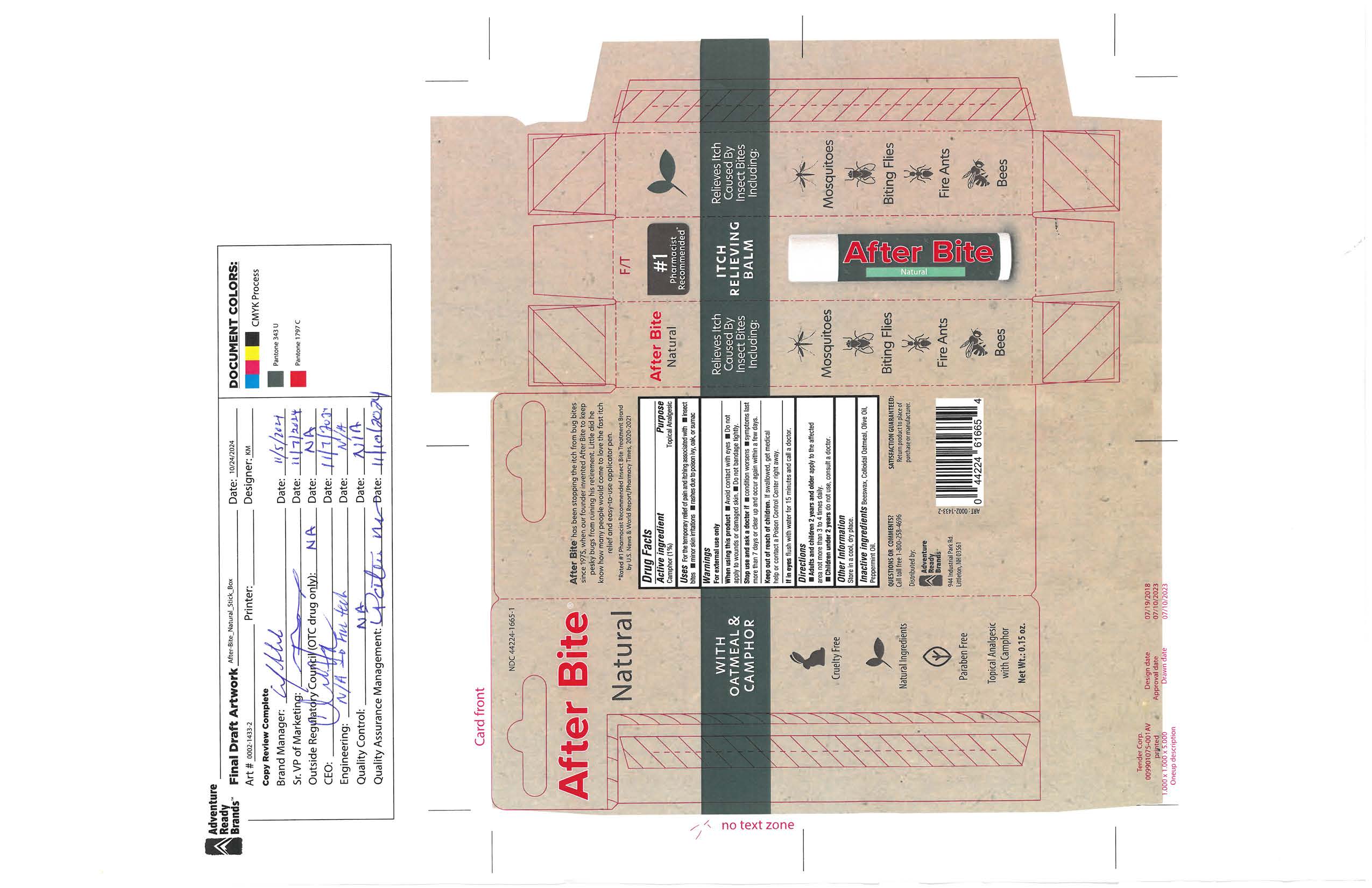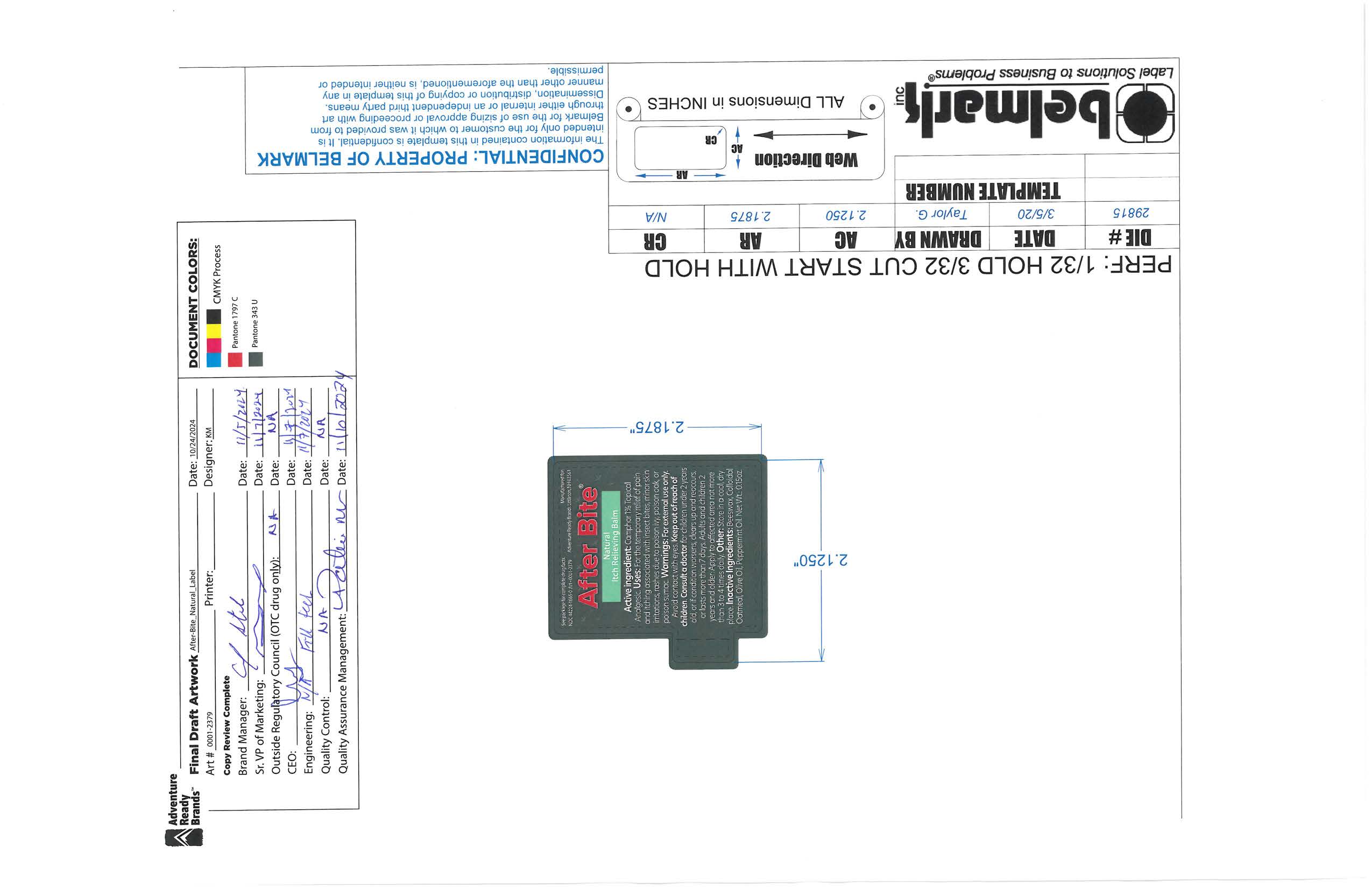 DRUG LABEL: After Bite Natural
NDC: 44224-1665 | Form: SALVE
Manufacturer: Tender Corporation d/b/a Adventure Ready Brands
Category: otc | Type: HUMAN OTC DRUG LABEL
Date: 20251114

ACTIVE INGREDIENTS: CAMPHOR (SYNTHETIC) 0.0425 g/4.25 g
INACTIVE INGREDIENTS: BEESWAX 0.95 g/4.25 g; OLIVE OIL 2.8 g/4.25 g; PEPPERMINT OIL 0.02125 g/4.25 g; OATMEAL 0.425 g/4.25 g

After Bite Natural Stick

Active Ingredient

Active Ingredient Purpose

Camphor (1%) Topical Analgesic

Purpose

Topical Analgesic

Uses

For temporary reelief of pain and itching associated with • insect bites • minor skin irritations • rashes due to poison ivy, oak, or sumac.

Warnings

For external use only

If in eyes flush with water for 15 minutes and call a doctor

When using this product• Avoid contact with eyes•Do no apply to wounds or damaged skin•Do not bandage tightly.

Stop use and ask a doctor if •condition worsens•symptoms last more than 7 days or clear up and occur again within a few days.

Keep out of reaach of children

Keep out of reach of children. If swollowed, get medical help or contact poison control center right away.

Directions

• Adults and children 2 years and older apply to affected area not more than 3 to 4 times daily.

Children under 2 years old

Children under 2 years do not use, consult a doctor

Other Information

Store in cool dry place.

Inactive ingredients

Inactive ingredients Beeswax, Colloidal Oatmeal, Olive Oil, Peppermint Oil.

Questions or Comments

Call toll free 1-800258-4696

After Bite Natural Primary Display Panel

Aftr Bite

Natural

#1

Pharmacist

Recommended

Itch

Relieveing

Balm

With Oatmeal &

Camphor

Cruelty Free

Natural Ingredients

Paraben Free

Topical Analgesic

with Camphor

Net Wt.: 0.15oz